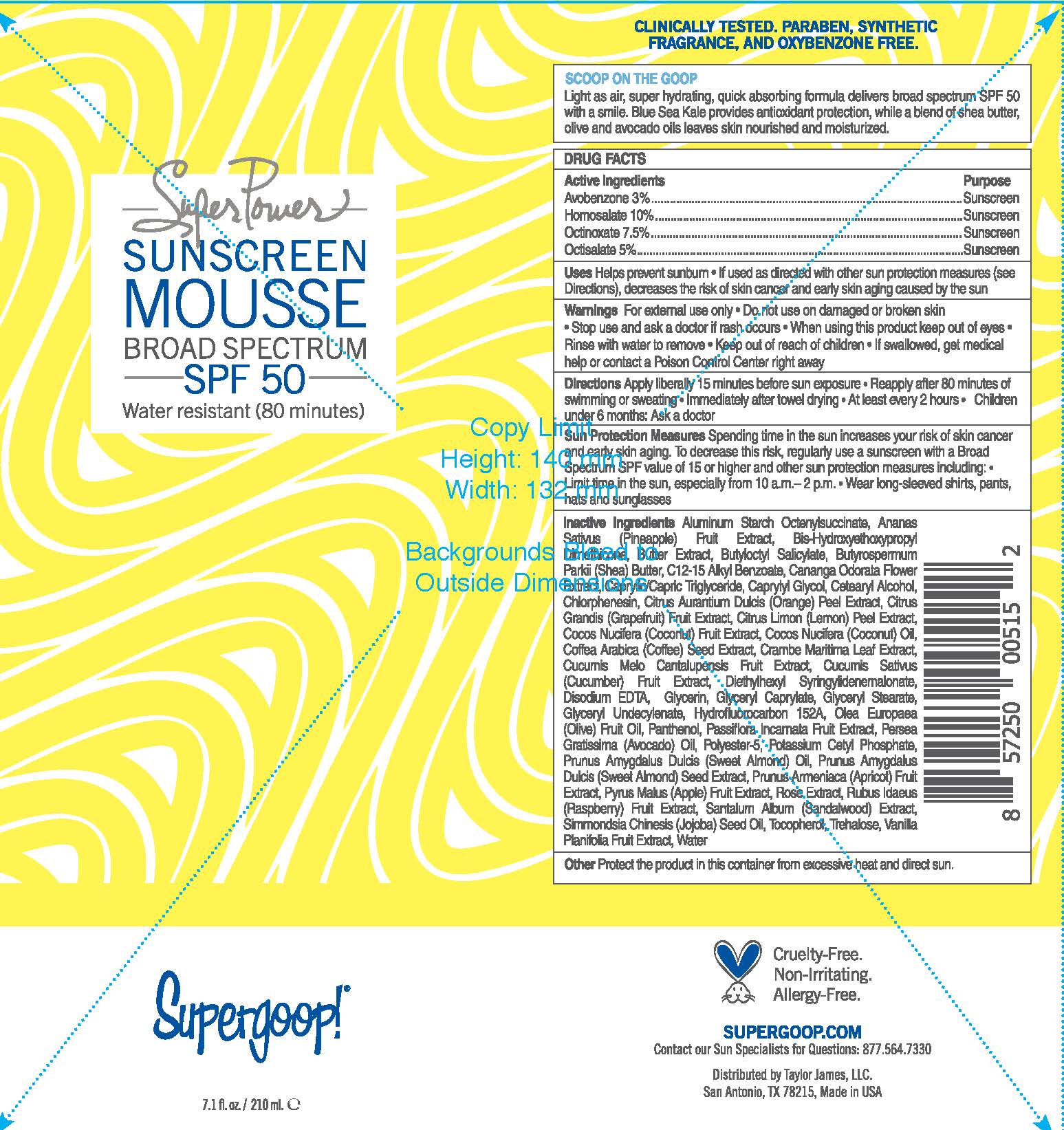 DRUG LABEL: Super Power Sunscreen Mousse SPF 50
NDC: 75936-505 | Form: CREAM
Manufacturer: TAYLOR JAMES, LTD.
Category: otc | Type: HUMAN OTC DRUG LABEL
Date: 20180207

ACTIVE INGREDIENTS: AVOBENZONE 3 kg/100 mL; HOMOSALATE 10 kg/100 mL; OCTINOXATE 7.5 kg/100 mL; OCTISALATE 5 kg/100 mL
INACTIVE INGREDIENTS: ALUMINUM STARCH OCTENYLSUCCINATE; PINEAPPLE; BIS-HYDROXYETHOXYPROPYL DIMETHICONE (37 CST); BUTYLOCTYL SALICYLATE; SHEA BUTTER; ALKYL (C12-15) BENZOATE; CANANGA ODORATA FLOWER; MEDIUM-CHAIN TRIGLYCERIDES; CAPRYLYL GLYCOL; CETOSTEARYL ALCOHOL; CHLORPHENESIN; ORANGE PEEL; GRAPEFRUIT; LEMON PEEL; COCONUT; COCONUT OIL; ARABICA COFFEE BEAN; CRAMBE MARITIMA LEAF; CANTALOUPE; CUCUMBER; DIETHYLHEXYL SYRINGYLIDENEMALONATE; EDETATE DISODIUM; GLYCERIN; GLYCERYL MONOCAPRYLATE; GLYCERYL MONOSTEARATE; GLYCERYL 1-UNDECYLENATE; 1,1-DIFLUOROETHANE; OLIVE OIL; PANTHENOL; PASSIFLORA INCARNATA FRUIT; AVOCADO OIL; POLYESTER-5 (TG-38); POTASSIUM CETYL PHOSPHATE; ALMOND OIL; ALMOND; APRICOT; APPLE; RASPBERRY; SANDALWOOD; JOJOBA OIL; TOCOPHEROL; TREHALOSE; VANILLA; WATER

Super Power Sunscreen Mousse SPF 50

Active Ingredients Purpose

Avobenzone 3% ....................... Sunscreen

Homosalate 10% ...................... Sunscreen

Octinoxate 7.5% ....................... Sunscreen

Octisalate 5% ........................... Sunscreen

Uses

Helps prevent sunburn

- If used as directed with other sun protection measures (see Direction), decreases the risk of skin cancer and early skin aging caused by the sun

Keep out of reach of children.

Stop use and ask a doctor if rash occurs

Warnings

For external use only

- Do not use on damaged or broken skin
- When using this product keep out of eyes
- Rinse with water to remove
- If swallowed, get medical help or contact a Poison Control Center right away

Directions

- Apply liberally 15 minutes before sun exposure
- Reapply after 80 minutes of swimming or sweating
- Immediately after towel drying
- At least every 2 hours
- Children under 6 months: Ask a doctor

Sun Protection Measures Spending time in teh sun increases your risk of skin cancer and early skin aging. To decrease this risk, regularly use a sunscreen with a Broad Spectrum SPF value of 15 or higher and other sun protection measures including:

- Limit time in the sun, especially from 10 a.m. - 2 p.m.
- Wear long-sleeved shirts, pants, hats, and sunglasses

INACTIVE INGREDIENT

Aluminum Starch Octenylsuccinate, Ananas Sativus (Pineapple) Fuit Extract, Bis-Hydroxyethoxypropyl Dimethicone, Butter Extract, Butyloctyl Salicylate, Butyrospermum Parkii (Shea) Butter, C12-15 Alkyl Benzoate, Cananga Odorata Flower Extract, Caprylic/Capric Triglyceride, Caprylyl Glycol, Cetearyl Alcohol, Chlorphenesin, Citrus Aurantium Dulcis (Orange) Peel Extract, Citrus Grandis (Grapefruit) Fruit Extract, Citrus Limon (Lemon) Peel Extract, Cocos Nucifera (Cocnut) Fruit Extract, Cocos Nucifera (Coconut) Oil, Arabica (Coffee) Seed Extract, Crambe Maritima Leaf Extract, Cucumis Melo Cantalupensis Fruit Extract, Cucumis Sativus (Cucumber) Fruit Extract, Diethylhexyl Syringylidenemalonate, Disodium EDTA, Glycerin, Glyceryl Caprylate, Glyceryl Stearate, Glyceryl Undecylenate, Hydrofluorocarbon 152A, Olea Europaea (Olive) Fruit Oil, Panthenol, Passiflora Incarnata Fruit Extract, Persea Gratissima (Avocado) Oil, Polyester-5, Potassium Cetyl Phosphate, Prunus Amygdalus Dulcis (Sweet Almond) Oil, Prunus Amygdalus Dulcis (Sweet Almond) Seed Extract, Prunus Armeniaca (Apricot) Fruit Extract, Pyrus Malus (Apple) Fruit Extract, Rose Extract, Rubus Idaeus (Raspberry) Fruit Extract, Santalum Album (Sandalwood) Extract, Simmondsia Chinesis (Jojoba) Seed Oil, Tocopherol, Trehalose, Vanilla Planifolia Fruit Extract, Water

PACKAGE LABEL

Super Power

Sunscreen

MOUSSE

Broad Spectrum SPF 50

Water resistant (80 minutes)

Supergoop!

7.1 fl. oz. / 200 mL